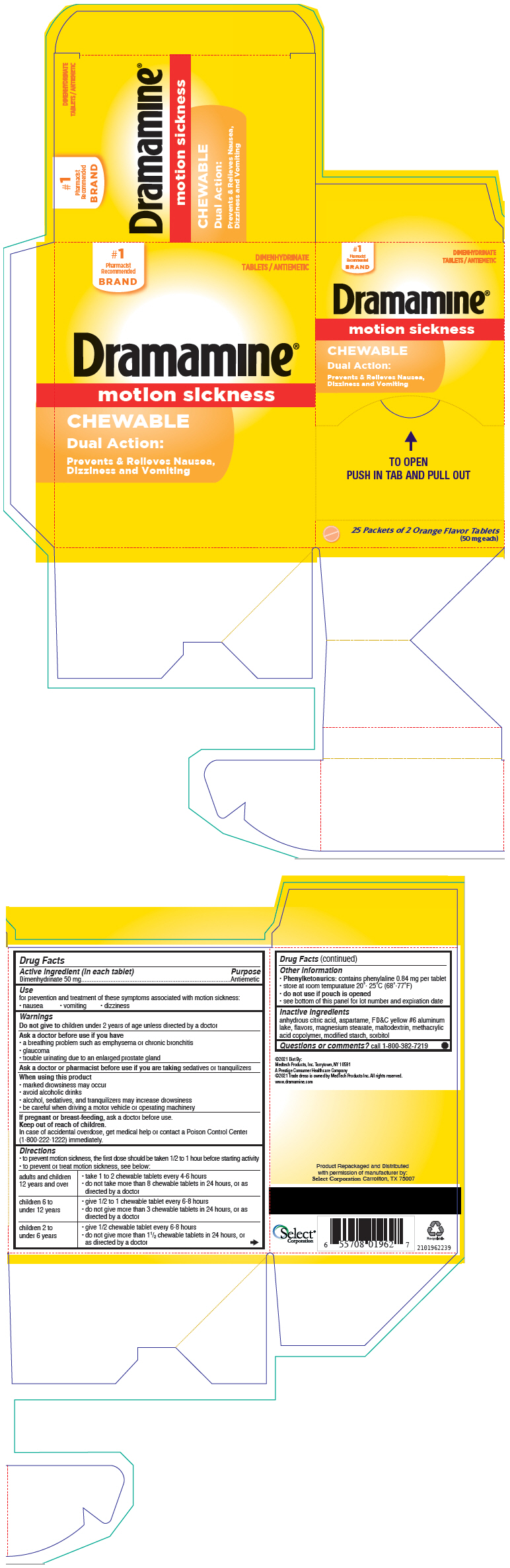 DRUG LABEL: Dramamine
NDC: 52904-962 | Form: TABLET
Manufacturer: Select Corporation
Category: otc | Type: HUMAN OTC DRUG LABEL
Date: 20220414

ACTIVE INGREDIENTS: DIMENHYDRINATE 50 mg/1 1
INACTIVE INGREDIENTS: silicon dioxide; croscarmellose sodium; lactose, unspecified form; magnesium stearate; MICROCRYSTALLINE CELLULOSE

Dramamine®

Drug Facts

Active ingredient (in each tablet)

Dimenhydrinate 50 mg

Purpose

Antiemetic

Use

for prevention and treatment of these symptoms associated with motion sickness:

- nausea
- vomiting
- dizziness

Warnings

Do not give to children under 2 years of age unless directed by a doctor

Ask a doctor before use if you have

- a breathing problem such as emphysema or chronic bronchitis
- glaucoma
- trouble urinating due to an enlarged prostate gland

Ask a doctor or pharmacist before use if you are taking sedatives or tranquilizers

When using this product

- marked drowsiness may occur
- avoid alcoholic drinks
- alcohol, sedatives, and tranquilizers may increase drowsiness
- be careful when driving a motor vehicle or operating machinery

PREGNANCY OR BREAST FEEDING

If pregnant or breast-feeding, ask a doctor before use.

Keep out of reach of children.

In case of accidental overdose, get medical help or contact a Poison Control Center (1-800-222-1222) immediately.

Directions

- to prevent motion sickness, the first dose should be taken 1/2 to 1 hour before starting activity
- to prevent or treat motion sickness, see below:

adults and children 12 years and over | - take 1 to 2 chewable tablets every 4-6 hours - do not take more than 8 chewable tablets in 24 hours, or as directed by a doctor
children 6 to under 12 years | - give 1/2 to 1 chewable tablet every 6-8 hours - do not give more than 3 chewable tablets in 24 hours, or as directed by a doctor
children 2 to under 6 years | - give 1/2 chewable tablet every 6-8 hours - do not give more than 1½ chewable tablets in 24 hours, or as directed by a doctor

Other information

- Phenylketonurics: contains phenylaline 0.84 mg per tablet
- store at room tempurature 20°- 25°C (68°-77°F)
- do not use if pouch is opened
- see bottom of this panel for lot number and expiration date

Inactive ingredients

anhydrous citric acid, aspartame, FD&C yellow #6 aluminum lake, flavors, magnesium stearate, maltodextrin, methacrylic acid copolymer, modified starch, sorbitol

Questions or comments?

call 1-800-382-7219

Dist By:
Medtech Products, Inc. Tarrytown, NY 10591

Product Repackaged and Distributed
with permission of manufacturer by:
Select Corporation Carrollton, TX 75007

PRINCIPAL DISPLAY PANEL - 50 mg Tablet Packet Carton

#1
Pharmacist
Recommended
BRAND

DIMENHYDRINATE
TABLETS / ANTIEMETIC

Dramamine®

motion sickness

CHEWABLE

Dual Action:

Prevents & Relieves Nausea,
Dizziness and Vomiting

TO OPEN
PUSH IN TAB AND PULL OUT

25 Packets of 2 Orange Flavor Tablets
(50 mg each)